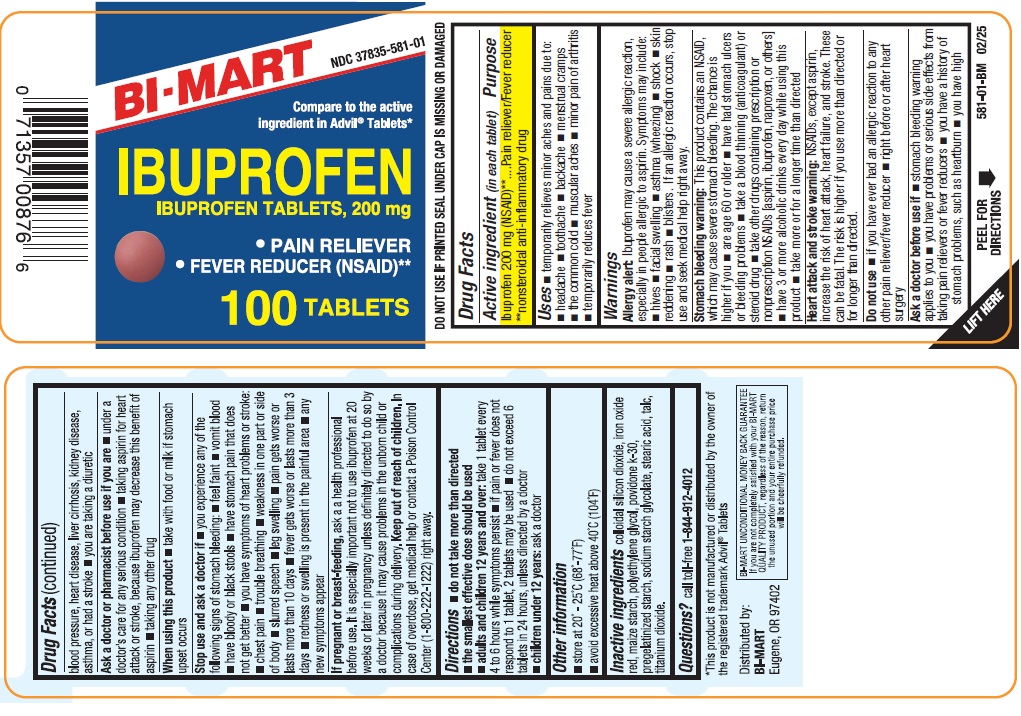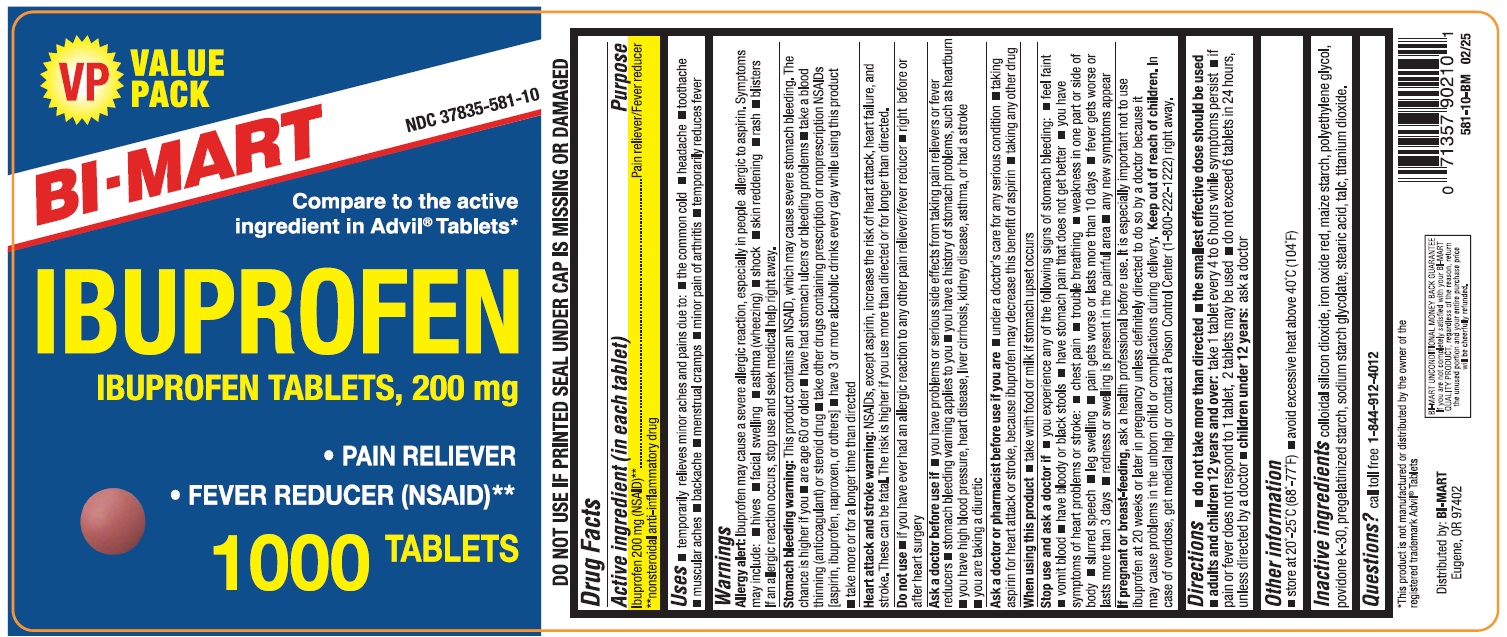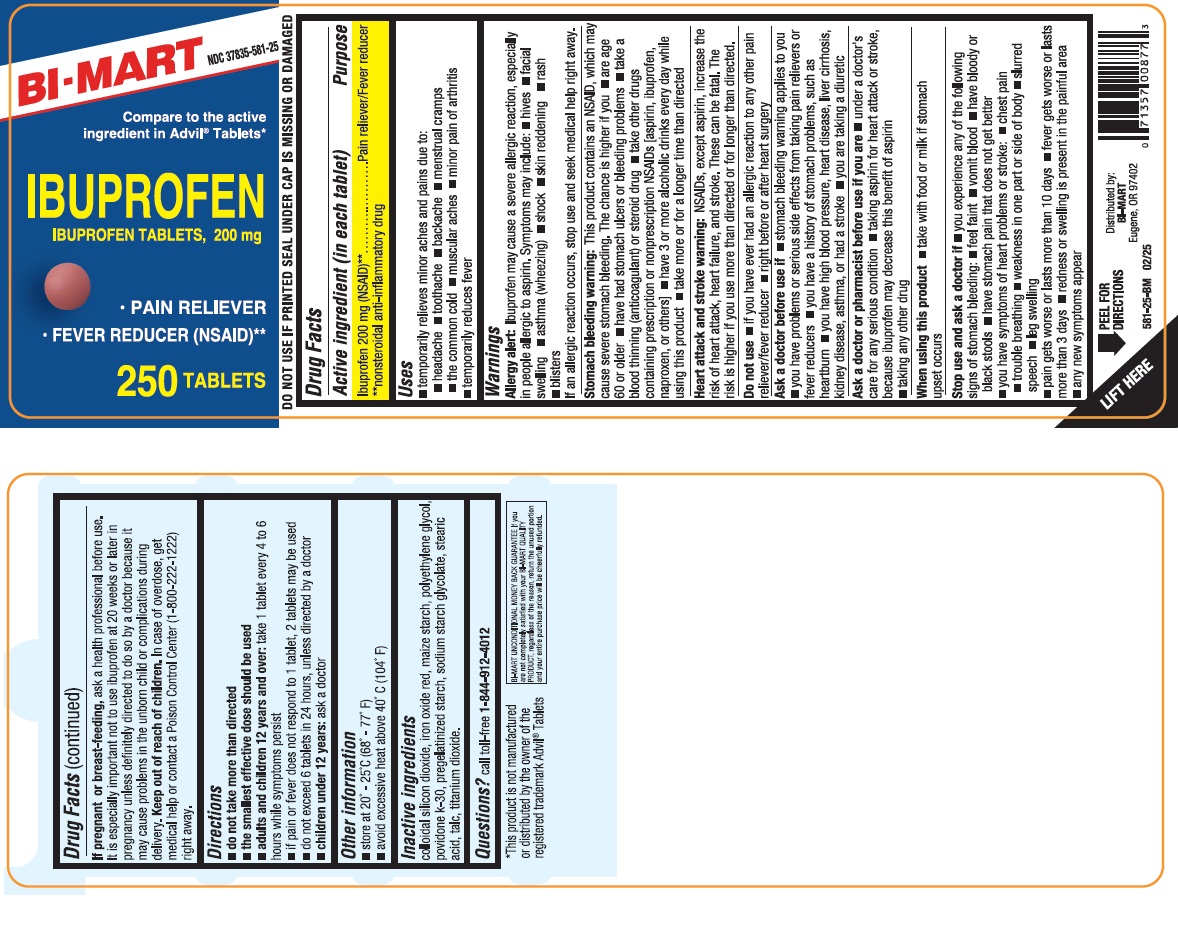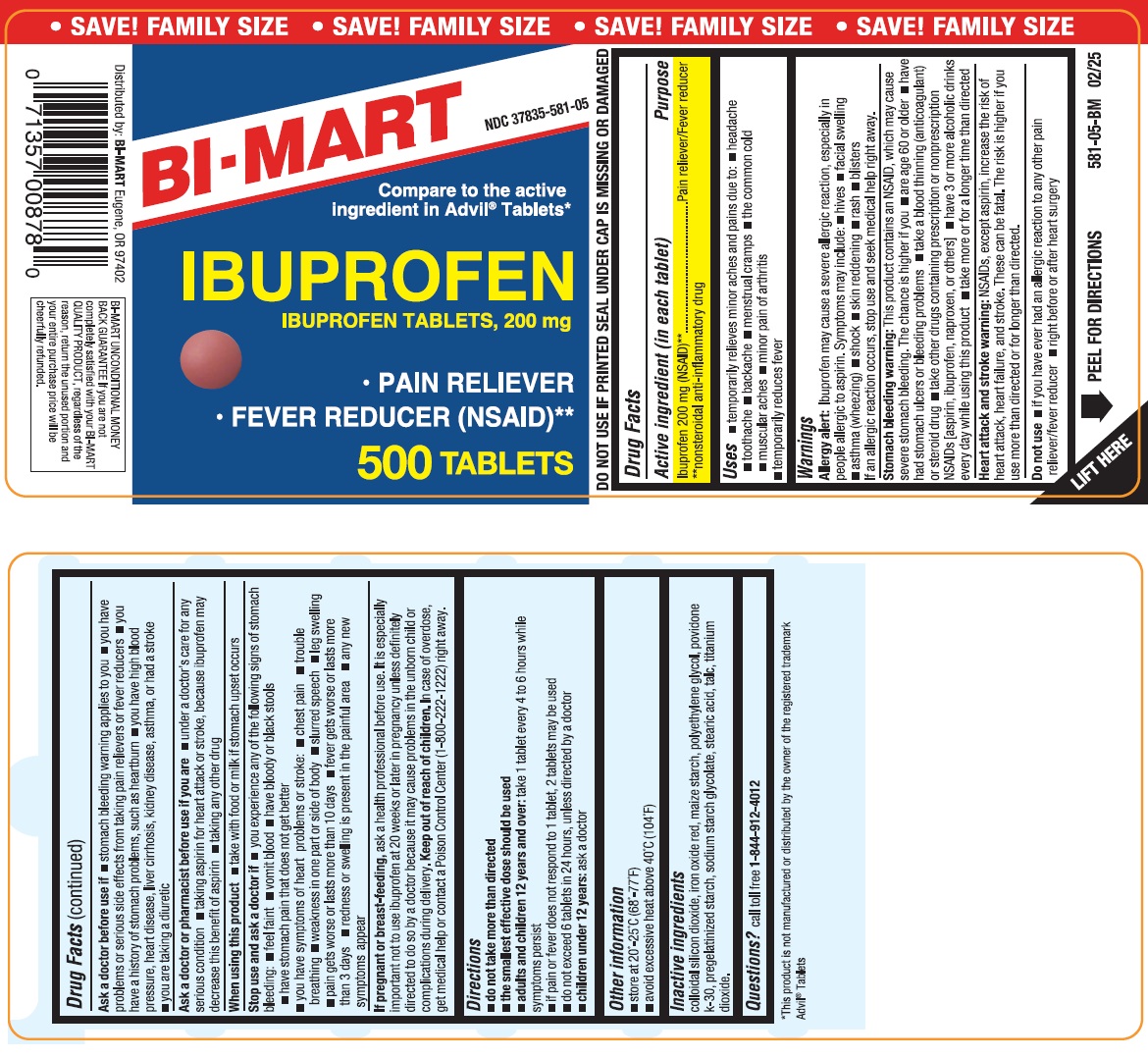 DRUG LABEL: Ibuprofen
NDC: 37835-581 | Form: TABLET
Manufacturer: Bi-Mart
Category: otc | Type: HUMAN OTC DRUG LABEL
Date: 20250201

ACTIVE INGREDIENTS: IBUPROFEN 200 mg/1 1
INACTIVE INGREDIENTS: SILICON DIOXIDE; FERRIC OXIDE RED; STARCH, CORN; POLYETHYLENE GLYCOL, UNSPECIFIED; POVIDONE K30; STEARIC ACID; SODIUM STARCH GLYCOLATE TYPE A POTATO; TALC; TITANIUM DIOXIDE

Ibuprofen Tablets, USP 200 mg

Drug Facts

ACTIVE INGREDIENT (in each tablet)

Ibuprofen 200 mg (NSAID)**

**nonsteroidal anti-inflammatory drug

PURPOSE

Pain reliever/ fever reducer

USES

- temporarily relieves minor aches and pains due to:
  - the common cold
  - headache
  - toothache
  - muscular aches
  - backache
  - menstrual cramps
  - minor pain of arthritis
- temporarily reduces fever

WARNINGS

Allergy alert:Ibuprofen may cause a severe allergic reaction, especially in people allergic to aspirin.
Symptoms may include:

- hives
- facial swelling
- asthma (wheezing)
- shock
- skin reddening
- rash
- blisters

If an allergic reaction occurs, stop use and seek medical help right away.

Stomach bleeding warning:

This product contains an NSAID, which may cause severe stomach bleeding.

The chance is higher if you:

- are age 60 or older
- have had stomach ulcers or bleeding problems
- take a blood thinning (anticoagulant) or steroid drug
- take other drugs containing prescription or nonprescription NSAIDs [aspirin, ibuprofen, naproxen, or others]
- have 3 or more alcoholic drinks every day while using this product
- take more or for a longer time than directed

Heart attack and stroke warning:
NSAIDs, except aspirin, increase the risk of heart attack, heart failure, and stroke. These can be fatal. The risk is higher if you use more than directed or for longer than directed.

DO NOT USE

- if you have ever had an allergic reaction to any other pain reliever/fever reducer
- right before or after heart surgery

ASK A DOCTOR BEFORE USE IF

- you have problems or serious side effects from taking pain relievers or fever reducers
- stomach bleeding warning applies to you
- you have a history of stomach problems, such as heartburn
- you have high blood pressure, heart disease, liver cirrhosis, kidney disease, asthma, or had a stroke
- you are taking a diuretic

ASK A DOCTOR OR PHARMACIST BEFORE USE IF YOU ARE

- under a doctor’s care for any serious condition
- taking aspirin for heart attack or stroke, because ibuprofen may decrease this benefit of aspirin
- taking any other drug

WHEN USING THIS PRODUCT

- take with food or milk if stomach upset occurs

STOP USE AND ASK A DOCTOR IF

- you experience any of the following signs of stomach bleeding:
- feel faint
- vomit blood
- have bloody or black stools
- have stomach pain that does not get better
- you have symptoms of heart problems or stroke:
- chest pain
- trouble breathing
- weakness in one part or side of body
- slurred speech
- leg swelling
- pain gets worse or lasts more than 10 days
- fever gets worse or lasts more than 3 days
- redness or swelling is present in the painful area
- any new symptoms appear

IF PREGNANT OR BREAST FEEDING,

ask a health professional before use. It is especially important not to use ibuprofen at 20 weeks or later in pregnancy unless definitely directed to do so by a doctor because it may cause problems in the unborn child or complications during delivery.

KEEP OUT OF REACH OF CHILDREN

In case of overdose, get medical help or contact a Poison Control Center (1-800-222-1222) right away.

DIRECTIONS

- do not take more than directed
- the smallest effective dose should be used
  adults and children 12 years and older | - take 1 tablet every 4 to 6 hours while symptoms persist - if pain or fever does not respond to 1 tablet, 2 tablets may be used - do not exceed 6 tablets in 24 hours, unless directed by a doctor
  children under 12 years | - ask a doctor

Other Information

- store at 20°-25°C (68°-77°F)
- avoid excessive heat above 40°C (104°F)
- DO NOT USE IF PRINTED SEAL UNDER CAP IS MISSING OR DAMAGED

INACTIVE INGREDIENTS

colloidal silicon dioxide, iron oxide red, maize starch, polyethylene glycol, povidone k-30, pregelatinized starch, sodium starch glycolate, stearic acid, talc, titanium dioxide.

QUESTIONS?

call toll free 1-844-912-4012

Distributed by:

BI-MART

Eugene, OR 97402

PACKAGE LABEL.PRINCIPAL DISPLAY PANEL

IBUPROFEN TABLETS USP, 200 mg

Compare to the active ingredients in Advil®Tablets*

*This product is not manufactured or distributed by the owner of the registered trademark Advil®Tablets.